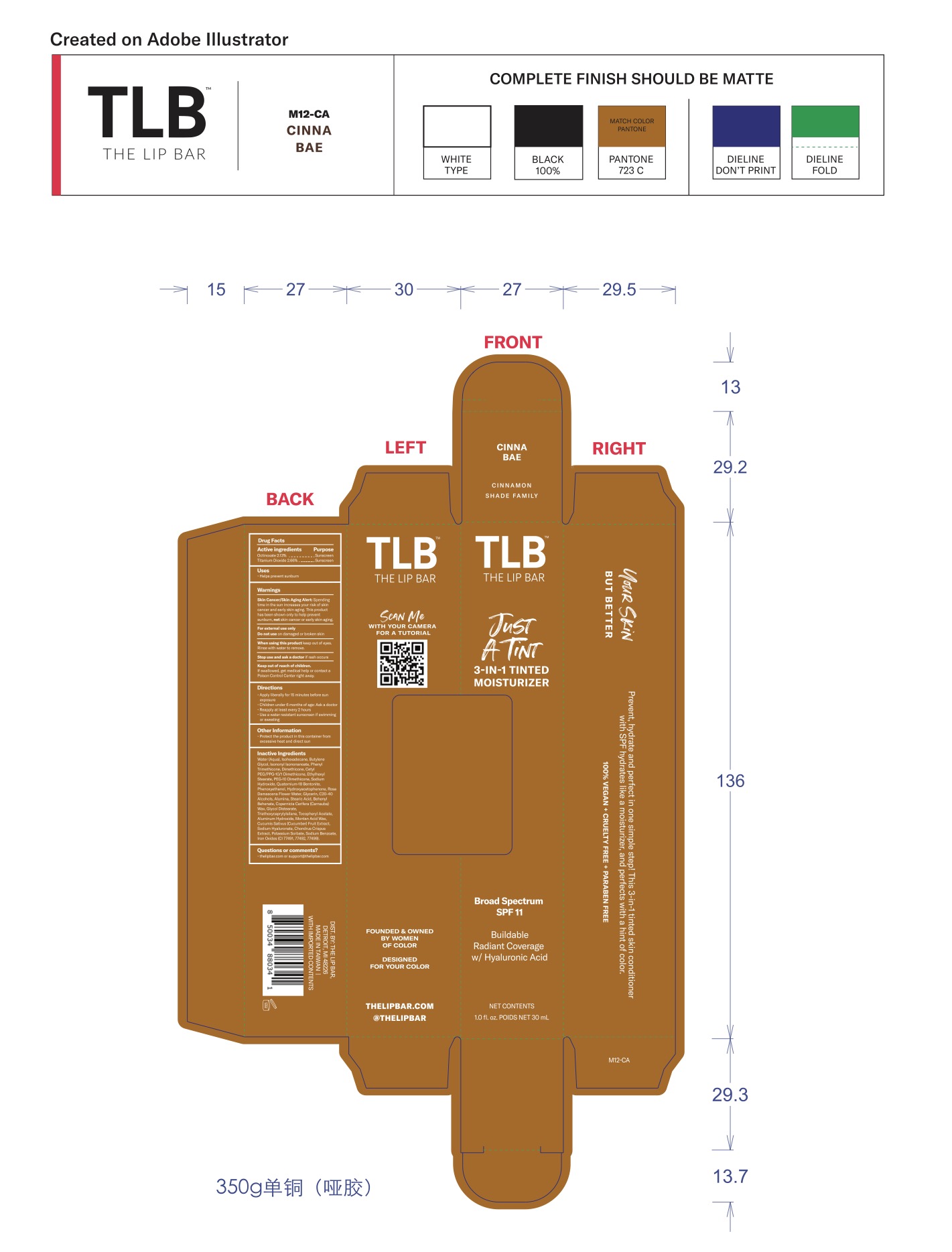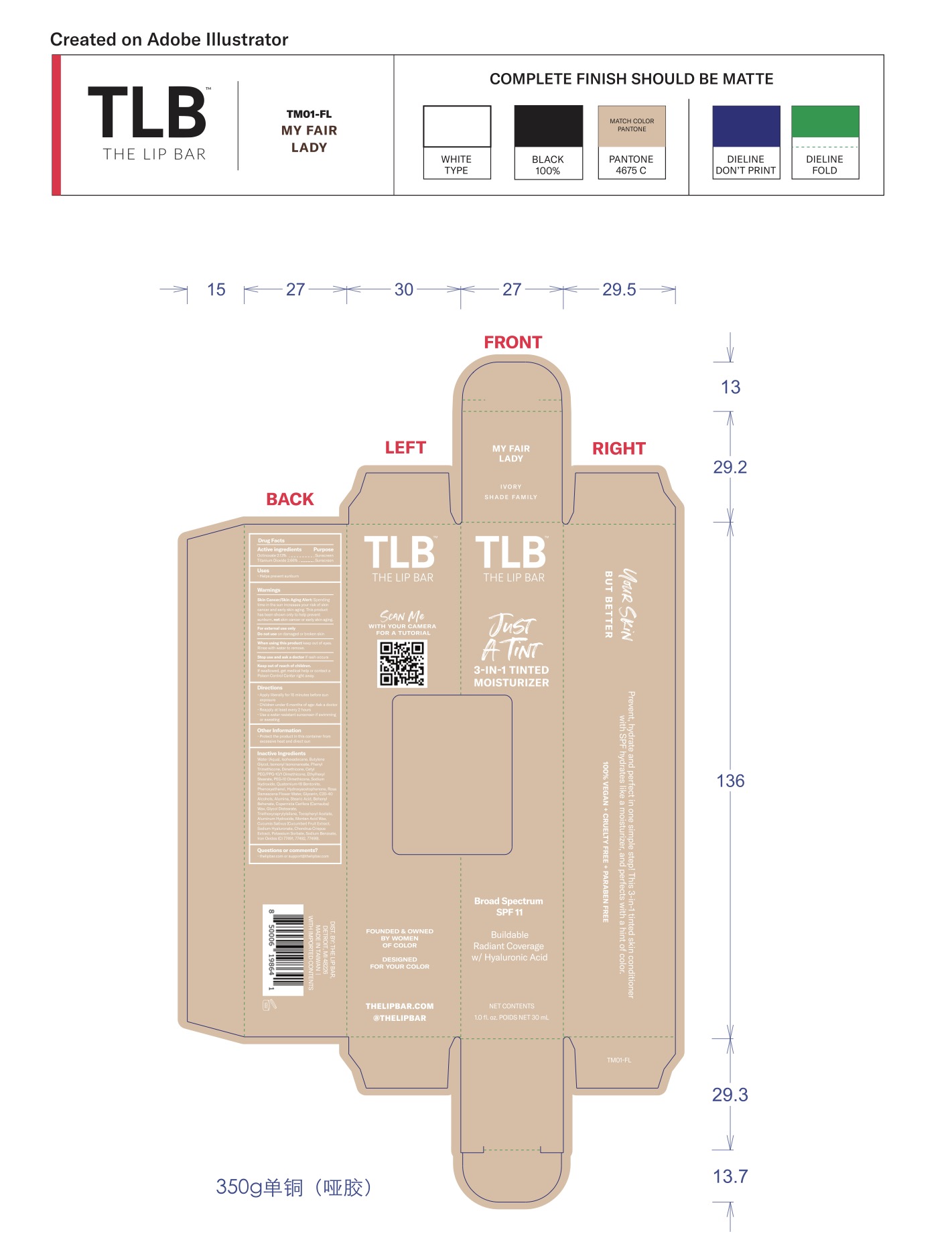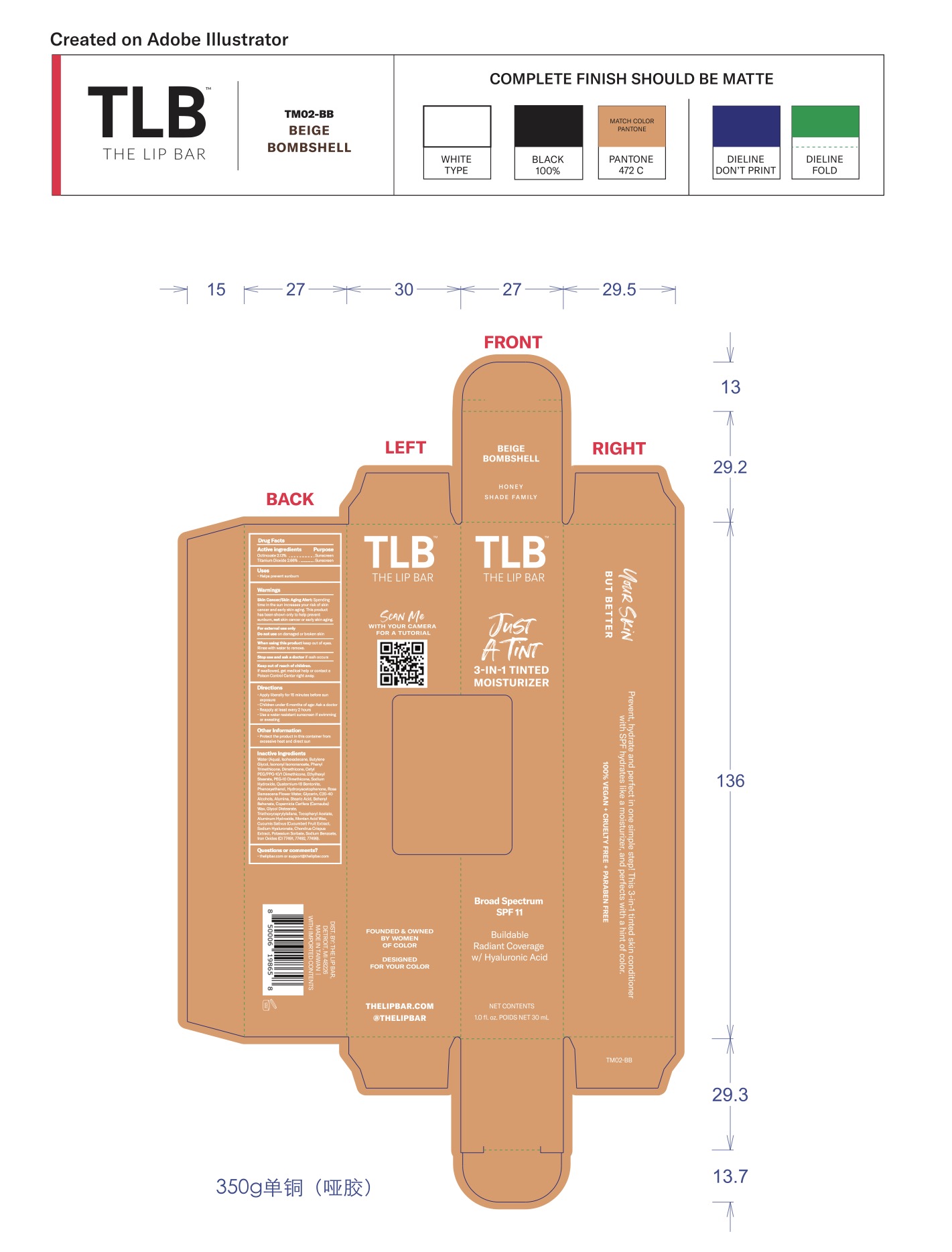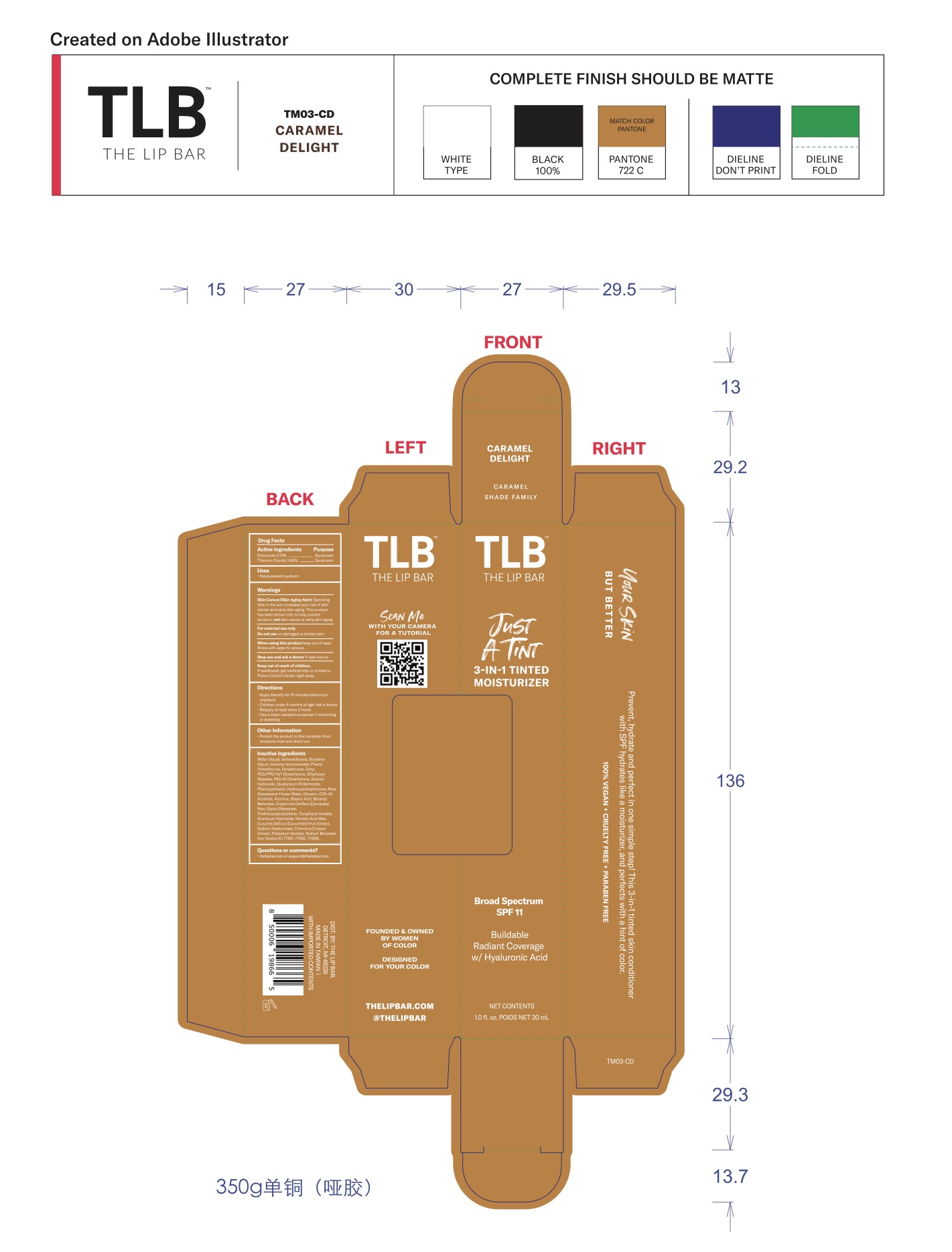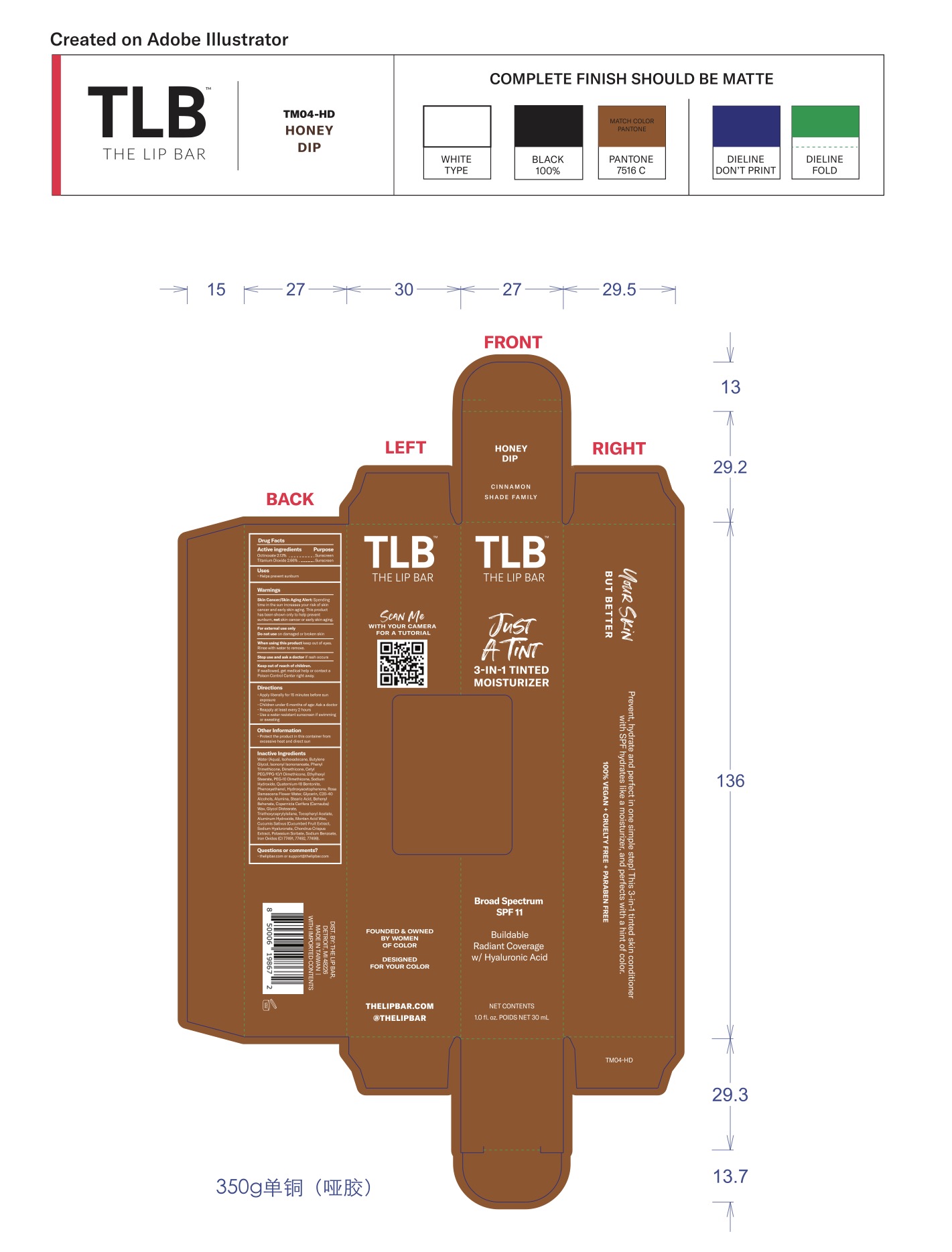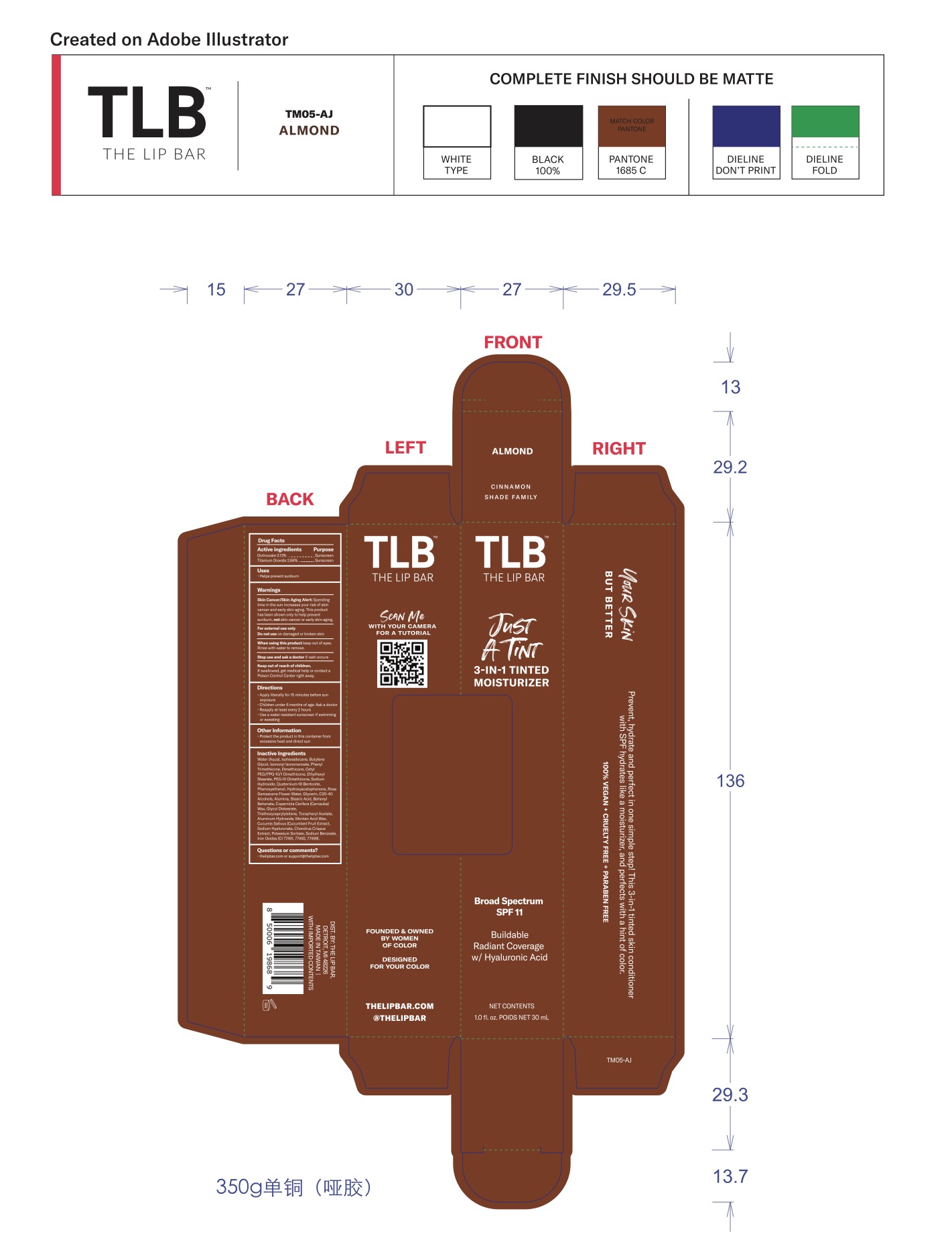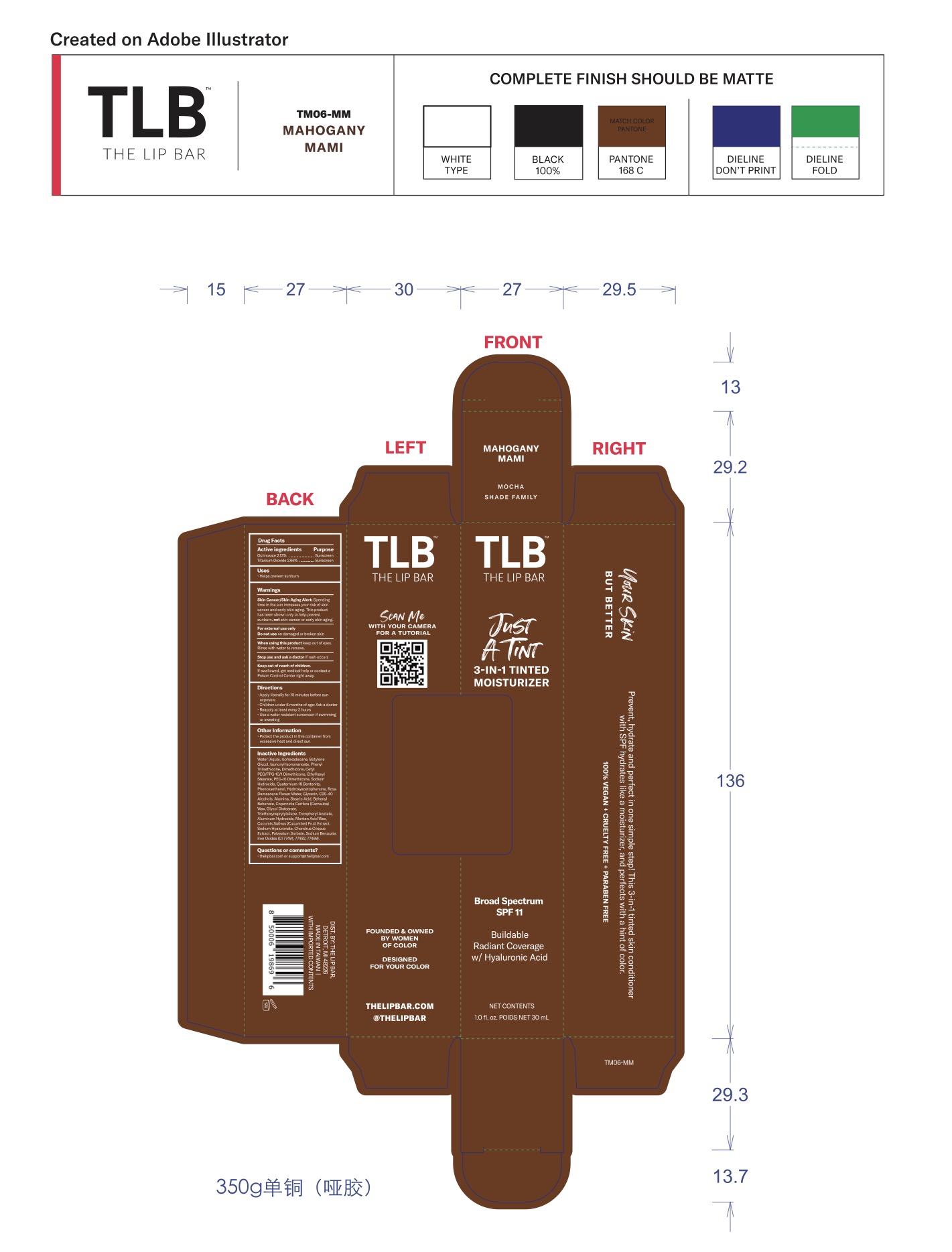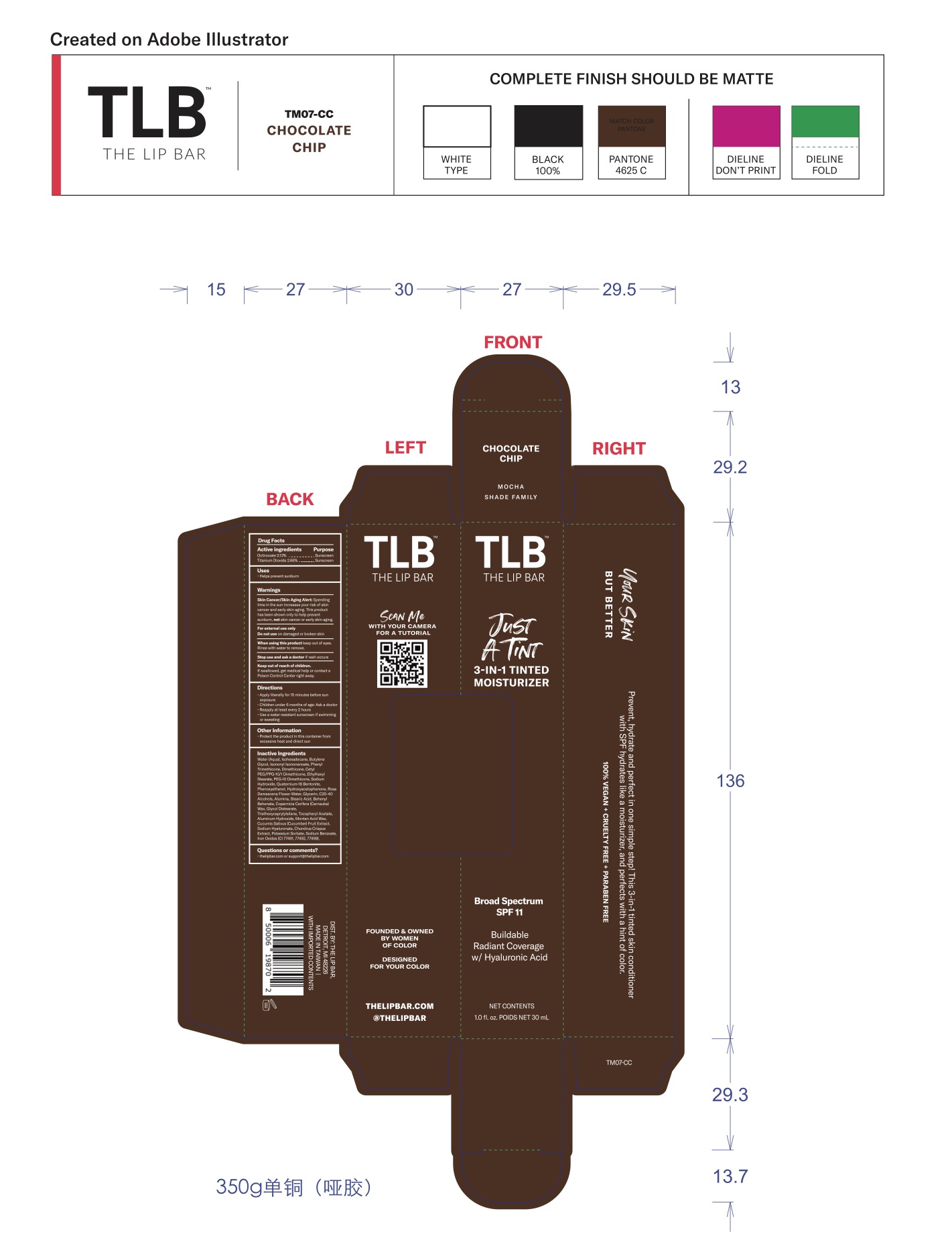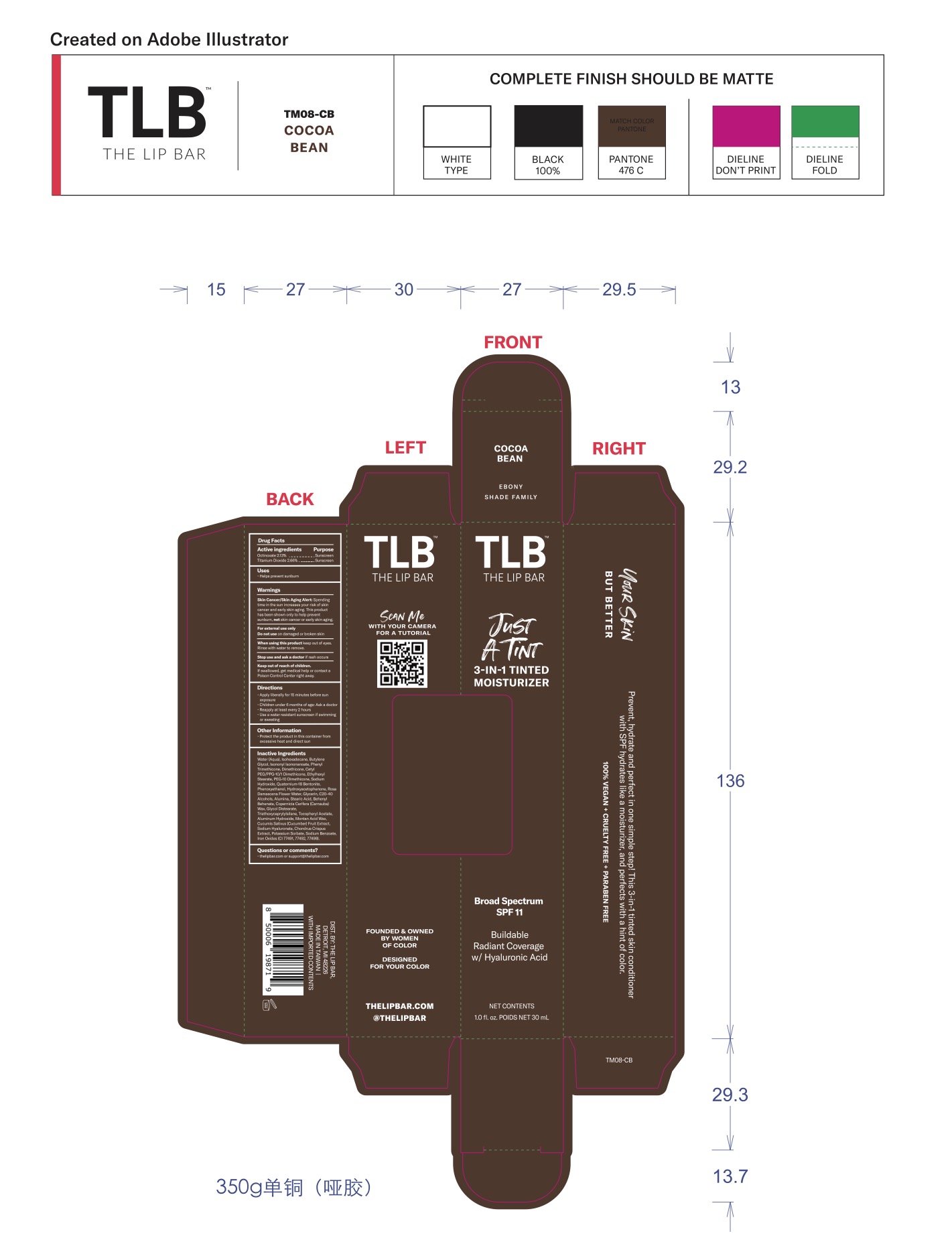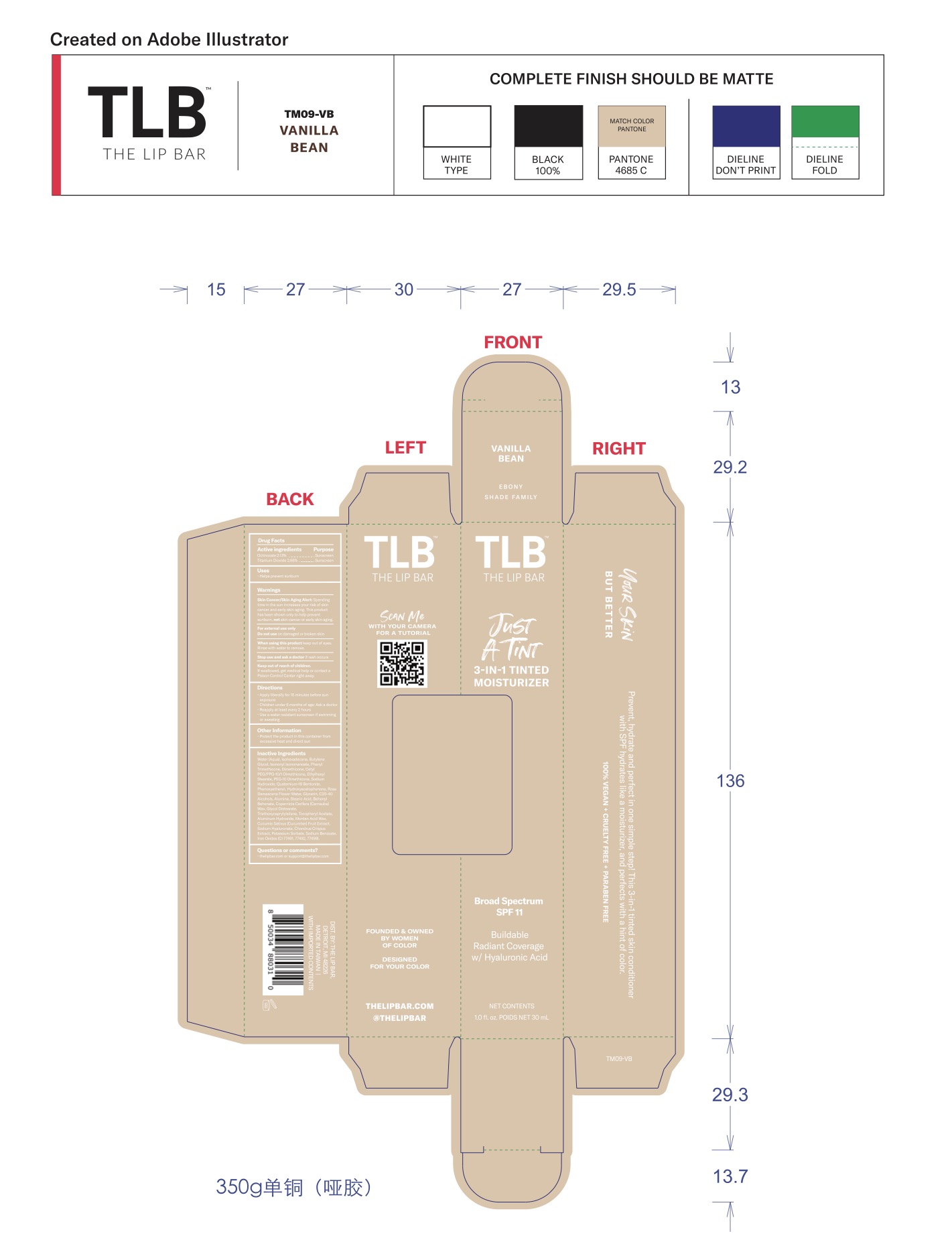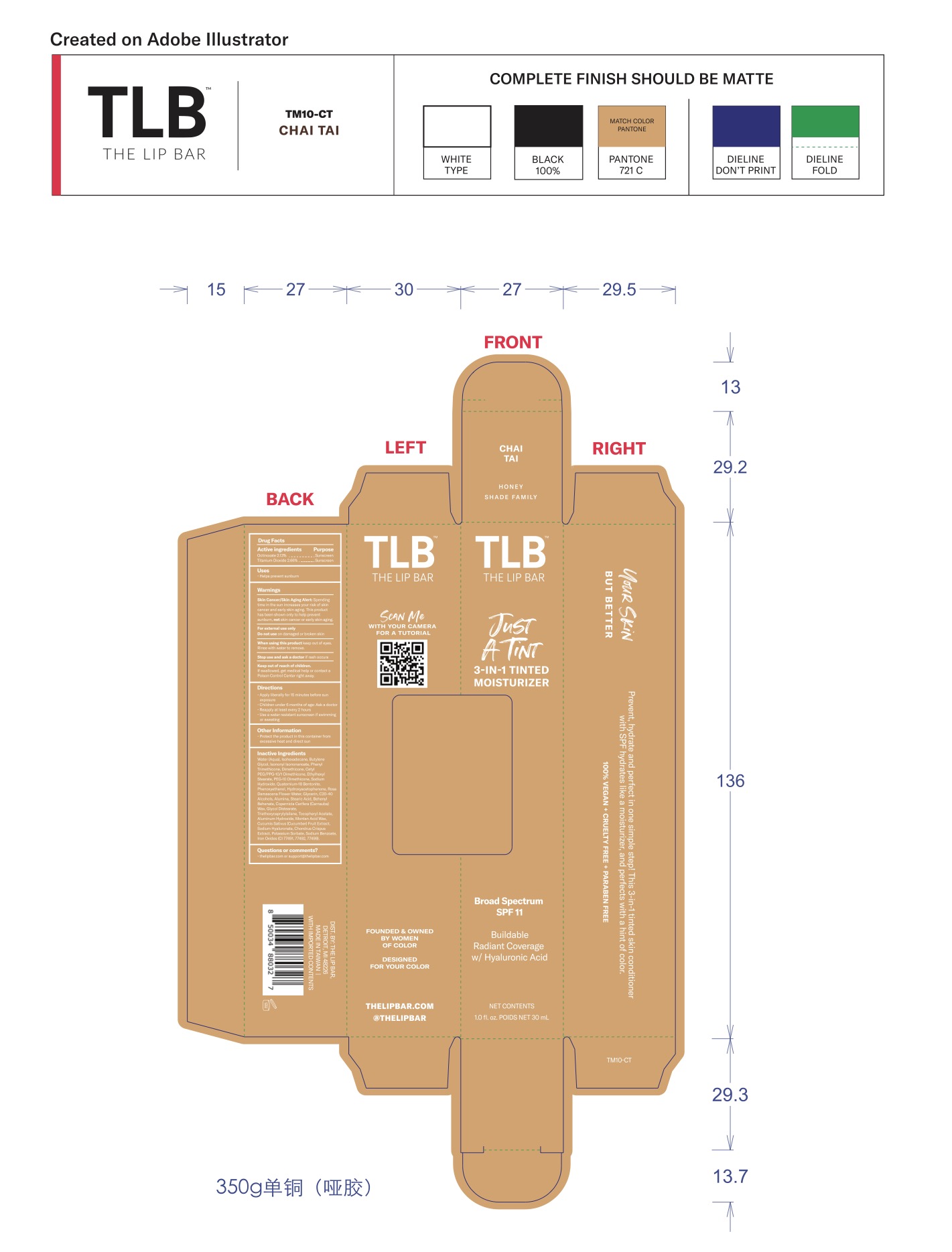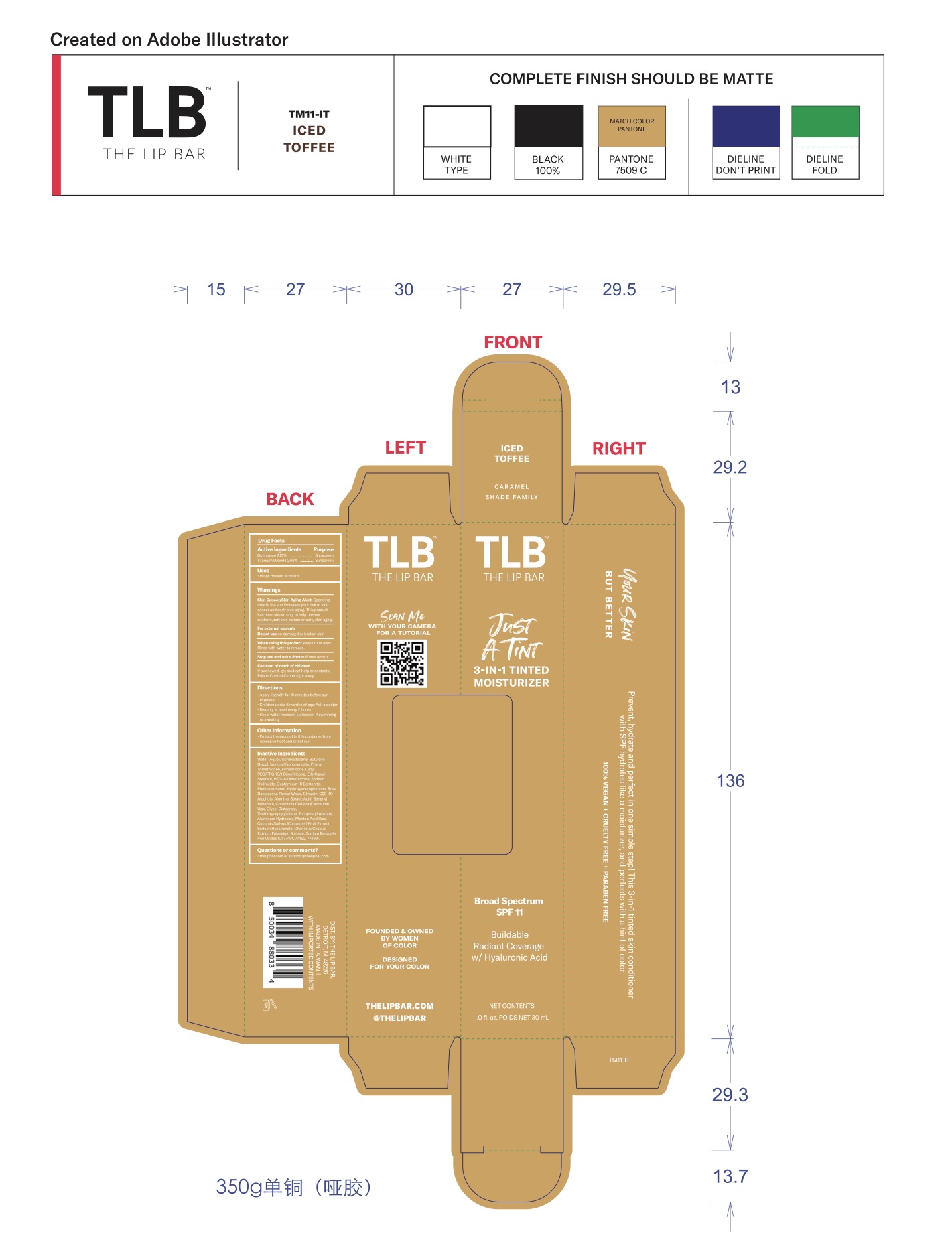 DRUG LABEL: Just a Tint 3-in-1 Tinted Skin Conditioner
NDC: 80817-114 | Form: CREAM
Manufacturer: The Lip Bar
Category: otc | Type: HUMAN OTC DRUG LABEL
Date: 20250301

ACTIVE INGREDIENTS: OCTINOXATE 21.3 mg/1 mL; TITANIUM DIOXIDE 26.6 mg/1 mL
INACTIVE INGREDIENTS: WATER

INACTIVE INGREDIENT

Water (Aqua), Isohexadecane, Butylene Glycol, Isononyl Isononanoate, Phenyl Trimethicone, Dimethicone, Cetyl PEG/PPG-10/1 Dimethicone, Ethylhexyl Stearate, PEG-10 Dimethicone, Sodium Hydroxide, Quaternium-18 Bentonite, Phenoxyethanol, Hydroxyacetophenone, Rosa Damascena Flower Water, Glycerin, C20-40 Alcohols, Alumina, Stearic Acid, Behenyl Behenate, Copernicia Cerifera (Carnauba) Wax, Glycol Distearate, Triethoxycaprylylsilane, Tocopheryl Acetate, Aluminum Hydroxide, Montan Acid Wax, Cucumis Sativus (Cucumber) Fruit Extract, Sodium Hyaluronate, Chondrus Crispus Extract, Potassium Sorbate, Sodium Benzoate, Iron Oxides (CI 77491, 77492, 77499).

Keep out of reach of children. If swallowed, get medical help or contact a poison control right away.

DOSAGE AND ADMINISTRATION

Apply liberally 15 minutes before sun exposure

Children under 6 months of age: Ask a doctor

Reapply at least every 2 hours

Use a water resistant sunscreen if swimming or sweating

INDICATIONS AND USAGE

Helps prevent sunburn

PURPOSE

helps prevent sunburn

WARNINGS

Skin Cancer/Skin Aging Alert: Spending time in the sun increases your risk of skin cancer and early skin aging. This product has been shown only to help prevent sunburn, not skin cancer or early skin aging.

For external use only

Do not use on damaged or broken skin

When using this product keep out of eyes. Rinse with water to remove.

Stop use and ask a doctor if rash occurs